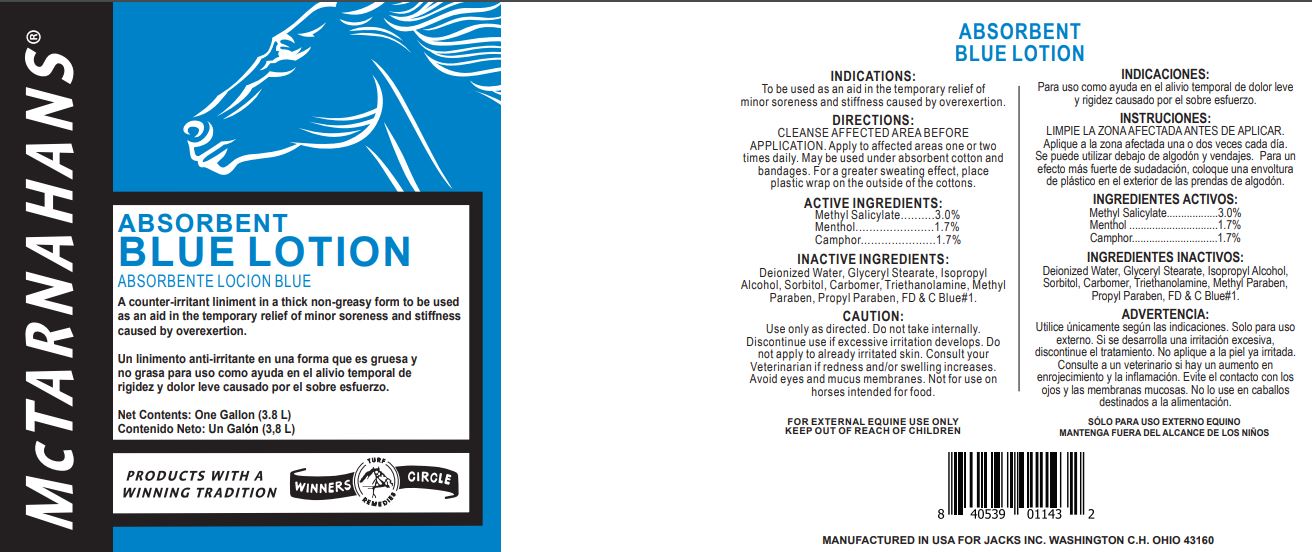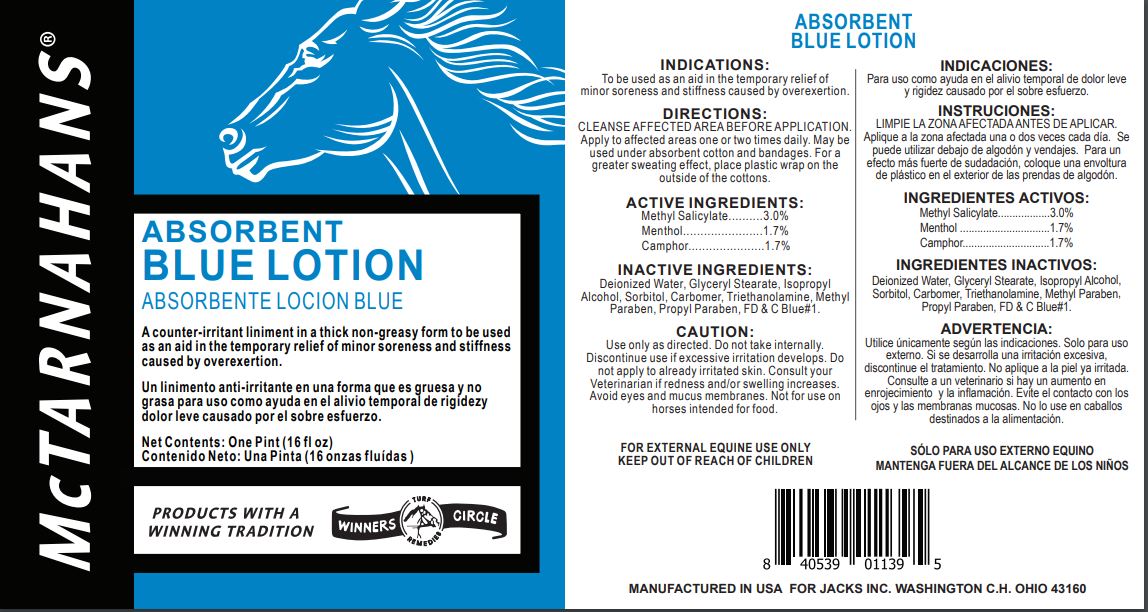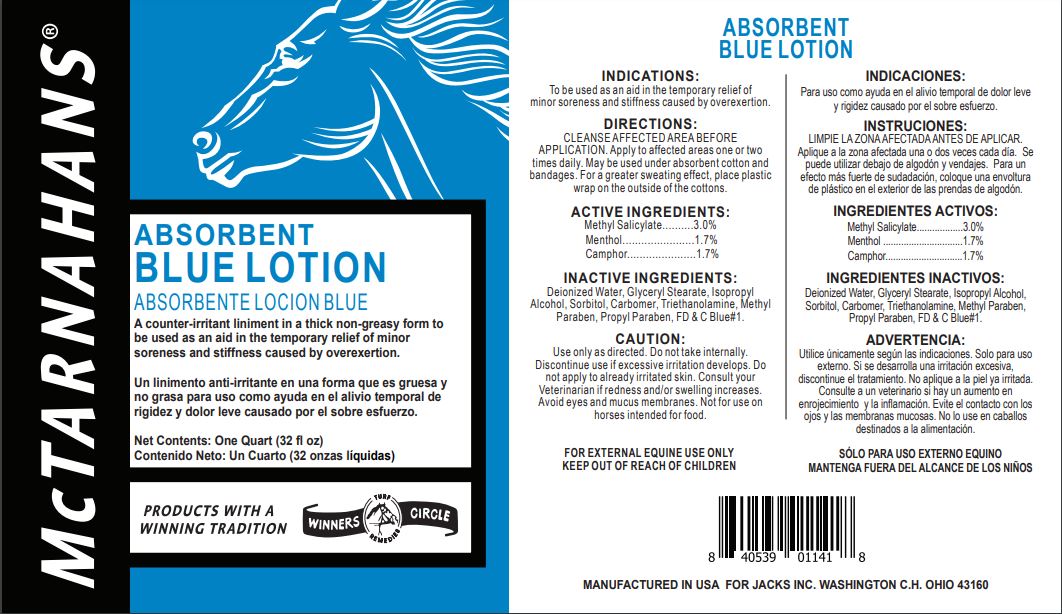 DRUG LABEL: Blue
NDC: 61156-202 | Form: LINIMENT
Manufacturer: JACKS MFG INC
Category: animal | Type: OTC ANIMAL DRUG LABEL
Date: 20211208

ACTIVE INGREDIENTS: METHYL SALICYLATE 0.0364 g/1 mL; MENTHOL 0.01688 g/1 mL; CAMPHOR (NATURAL) 0.01688 g/1 mL
INACTIVE INGREDIENTS: PROPYLPARABEN 0.00039 g/1 mL; METHYLPARABEN 0.00145 g/1 mL; CARBOMER 934 0.0017 g/1 mL; FD&C BLUE NO. 1 0.00003 g/1 mL; SORBITOL 0.03433 mL/1 mL; GLYCERYL STEARATE SE 0.0421 g/1 mL; TROLAMINE 0.0026 g/1 mL; ISOPROPYL ALCOHOL 0.0042 mL/1 mL; WATER 0.8425 mL/1 mL

BLUE LOTION

INDICATIONS

To be used as an aid in the temporary relief of minor soreness and stiffness caused by overexertion.

DIRECTIONS

CLEANSE AFFECTED AREA BEFORE APPLICATION.
Apply to affected areas one or two times daily.
May be used under absorbent cotton and bandages.
For a greater sweating effect, place plastic wrap on the outside of the cottons.

CAUTION

Use only as directed.
Do not take internally.
Discontinue use if excessive irritation develops.
Do not apply to already irritated skin.
Consult your Veterinarian if redness and/or swelling increases.
Avoid eyes and mucus membranes.
Not for use on horses intended for food.

FOR EXTERNAL EQUINE USE ONLY
KEEP OUT OF REACH OF CHILDREN